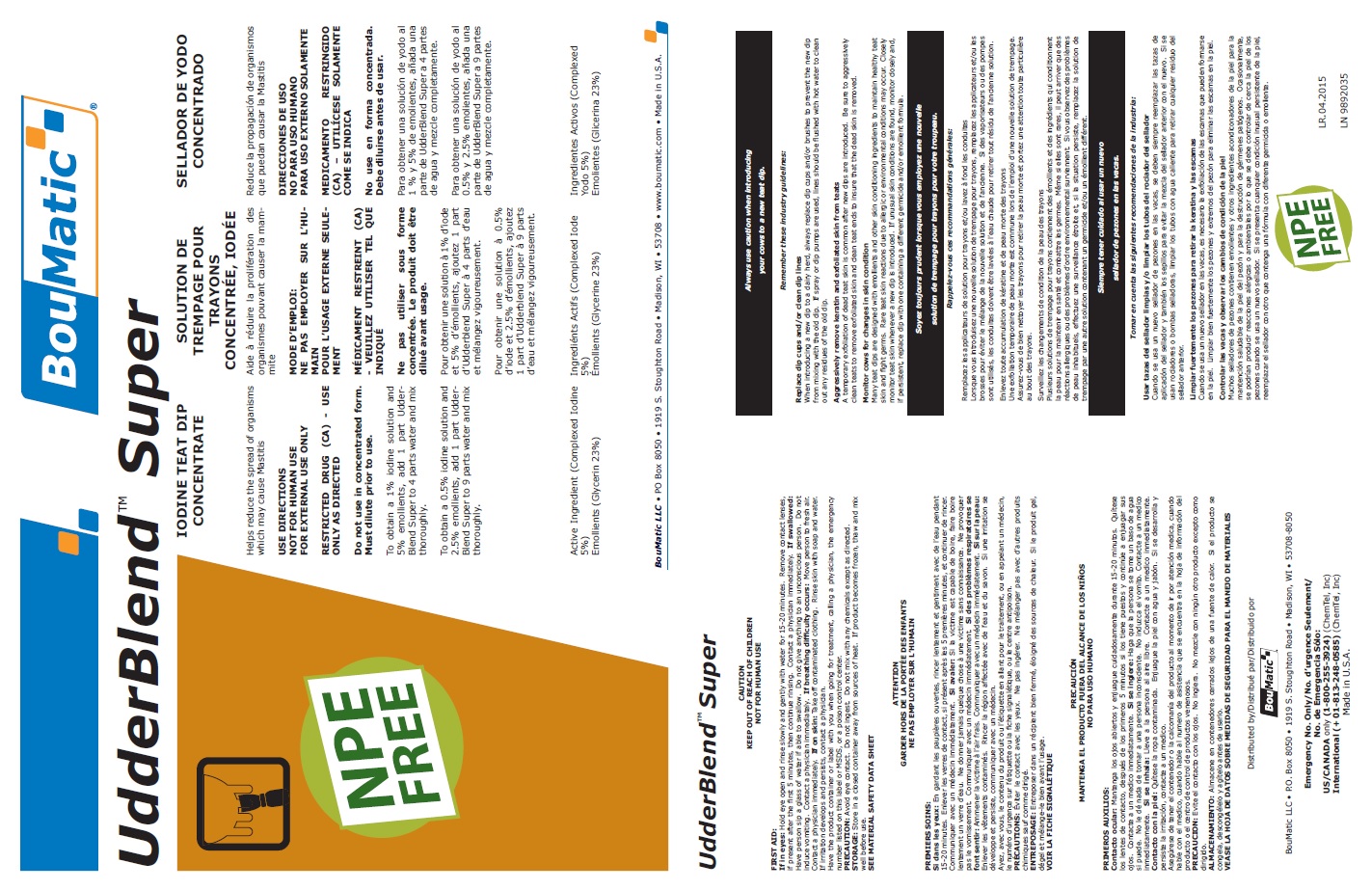 DRUG LABEL: Udderblend Super NPE Free
NDC: 48106-2027 | Form: LIQUID
Manufacturer: BouMatic, LLC
Category: animal | Type: OTC ANIMAL DRUG LABEL
Date: 20240614

ACTIVE INGREDIENTS: IODINE 55 g/1 L

Udderblend Super NPE Free

WARNINGS AND PRECAUTIONS

CAUTION

KEEP OUT OF REACH OF CHILDREN

NOT FOR HUMAN USE

FIRST AID:

If in eyes:

Hold eye open and rinse slowly and gently with water for 15-20 minutes. Remove contact lenses, if present after the first 5 minutes, then continue rinsing. Contact a physician immediately. If swallowed: Have person sip a glass of water if able to swallow. Do not give anything to an unconscious person. Do not induce vomiting. Contact a physician immediately. If breathing difficulty occurs: Move person to fresh air. Contact a physician immediately. If on skin: Take off contaminated clothing. Rinse skin with soap and water. If irritation develops and persists, contact a physician.

Have the product container or label with you when going for treatment, calling a physician, the emergency number listed on this label or MSDS, or a poison control center.

PRECAUTION:

Avoid eye contact. Do not ingest. Do not mix with any chemicals except as directed.

STORAGE:

Store in a closed container away from sources of heat. If product becomes frozen, thaw and mix well before use.

SEE MATERIAL SAFETY DATA SHEET

INDICATIONS AND USAGE

Iodine Teat Dip Concentrate

Helps reduce the spread of organisms which may cause Mastitis

USE DIRECTIONS

NOT FOR HUMAN USE

FOR EXTERNAL USE ONLY

RESTRICTED DRUG (CA) - USE ONLY AS DIRECTED

Do not use in concentrated form. Must dilute prior to use.

To obtain a 1% iodine solution and 5% emollients, add 1 part UdderBlend Super to 4 parts water and mix thoroughly.

To obtain a 0.5% iodine solution and 2.5% emollients, add 1 part UdderBlend Super to 9 parts water and mix thoroughly.

Active Ingredient (Complexed Iodine 5%)

Emollients (Glycerin 23%)